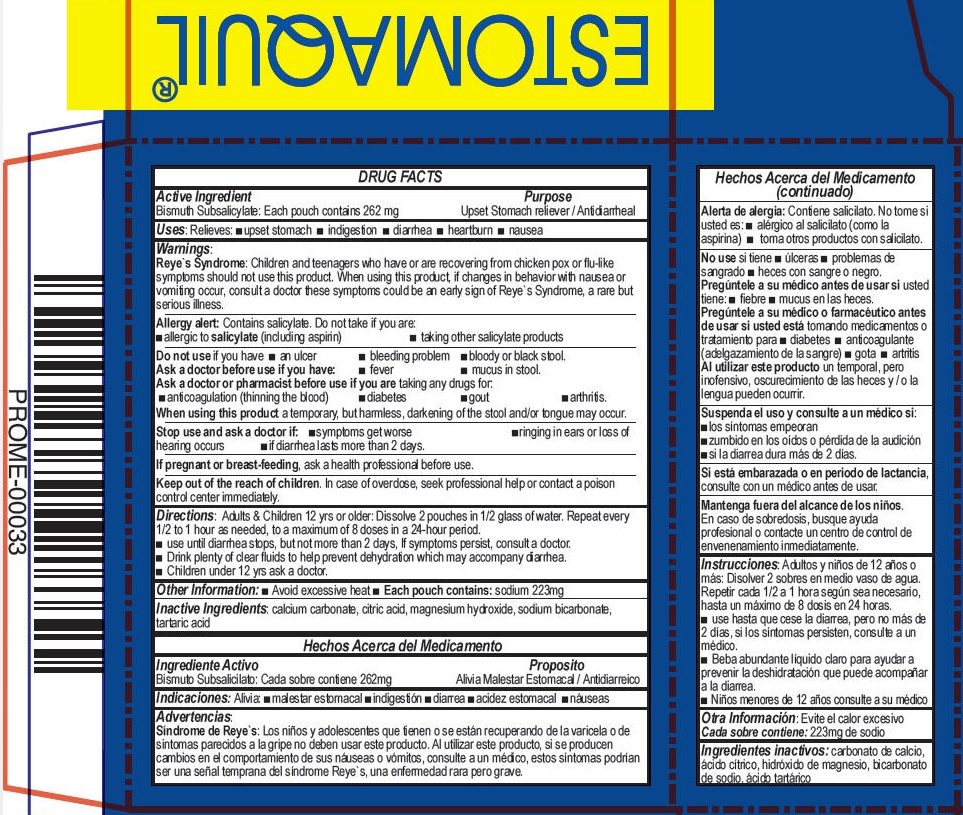 DRUG LABEL: Estomaquil Polvo
NDC: 51769-108 | Form: POWDER
Manufacturer: All Natural Dynamics	
Category: otc | Type: HUMAN OTC DRUG LABEL
Date: 20220627

ACTIVE INGREDIENTS: BISMUTH SUBSALICYLATE 262 mg/1 1
INACTIVE INGREDIENTS: CALCIUM CARBONATE; CITRIC ACID MONOHYDRATE; MAGNESIUM HYDROXIDE; SODIUM BICARBONATE; TARTARIC ACID

Estomaquil® Polvo

DRUG FACTS

Active Ingredient

Bismuth Subsalicylate: Each pouch contains 262 mg

Purpose

Upset Stomach reliever / Antidiarrheal

Uses

Relieves:

- upset stomach
- indigestion
- diarrhea
- heartburn
- nausea

Warnings

Reye`s Syndrome

Children and teenagers who have or are recovering from chicken pox or flu-like symptoms should not use this product. When using this product, if changes in behavior with nausea or vomiting occur, consult a doctor these symptoms could be an early sign of Reye`s Syndrome, a rare but serious illness.

Allergy alert

Contains salicylate. Do not take if you are:

- allergic to salicylate (including aspirin)
- taking other salicylate products

Do not use if you have

- an ulcer
- bleeding problem
- bloody or black stool.

Ask a doctor before use if you have

- fever
- mucus in stool.

Ask a doctor or pharmacist before use if you are taking any drugs for:

- anticoagulation (thinning the blood)
- diabetes
- gout
- arthritis.

When using this product a temporary, but harmless, darkening of the stool and/or tongue may occur.

Stop use and ask a doctor if

- symptoms get worse
- ringing in ears or loss of hearing occurs
- if diarrhea lasts more than 2 days.

PREGNANCY OR BREAST FEEDING

If pregnant or breast-feeding, ask a health professional before use.

KEEP OUT OF REACH OF CHILDREN

Keep out of the reach of children. In case of overdose, seek professional help or contact a poison control center immediately.

Directions

Adults & Children 12 yrs or older: Dissolve 2 pouches in 1/2 glass of water. Repeat every 1/2 to 1 hour as needed, to a maximum of 8 doses in a 24-hour period.

- use until diarrhea stops, but not more than 2 days, If symptoms persist, consult a doctor.
- Drink plenty of clear fluids to help prevent dehydration which may accompany diarrhea.
- Children under 12 yrs ask a doctor.

Other Information

- Avoid excessive heat
- Each pouch contains: sodium 223mg

Inactive Ingredients

calcium carbonate, citric acid, magnesium hydroxide, sodium bicarbonate, tartaric acid

PRINCIPAL DISPLAY PANEL - 10 Packet Carton

ESTOMAQUIL®

Relief for:

- Nausea
- Heartburn
- Diarrhea
- Fullness

Maximum Strength

10 Packets